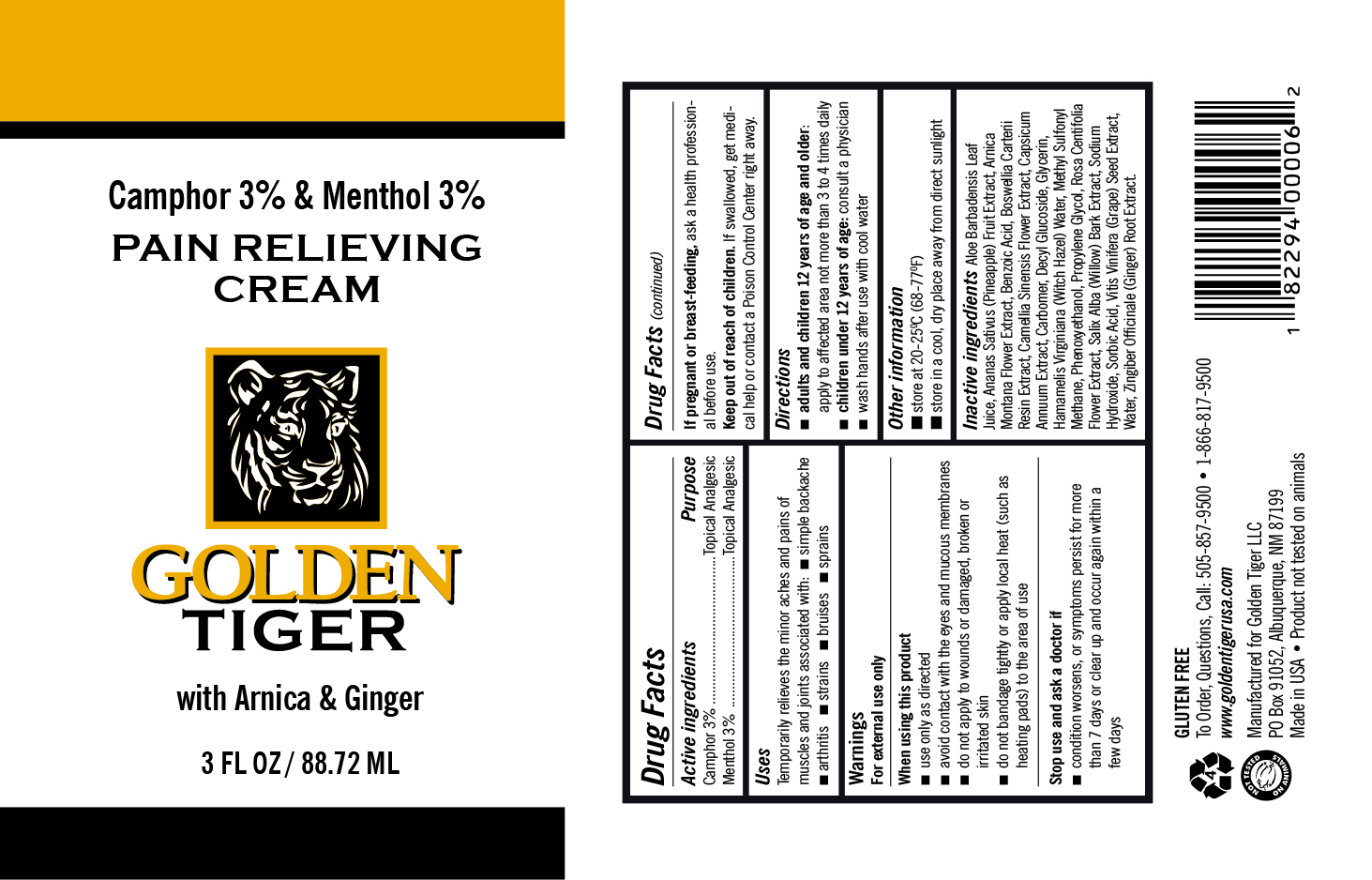 DRUG LABEL: Pain Relieving Cream
NDC: 84334-000 | Form: CREAM
Manufacturer: GOLDEN TIGER DISTRIBUTION L.L.C.
Category: otc | Type: HUMAN OTC DRUG LABEL
Date: 20241106

ACTIVE INGREDIENTS: MENTHOL 3 mg/100 mL; CAMPHOR (SYNTHETIC) 3 mg/100 mL
INACTIVE INGREDIENTS: PROPYLENE GLYCOL; ROSA CENTIFOLIA FLOWER; SALIX ALBA BARK; FRANKINCENSE; CAPSICUM; SODIUM HYDROXIDE; VITIS VINIFERA SEED; SORBIC ACID; PHENOXYETHANOL; GLYCERIN; CAMELLIA SINENSIS FLOWER; WATER; DIMETHYL SULFONE; DECYL GLUCOSIDE; GINGER; CARBOMER HOMOPOLYMER TYPE C (ALLYL PENTAERYTHRITOL CROSSLINKED); ARNICA MONTANA FLOWER; BENZOIC ACID; ANANAS SATIVUS (PINEAPPLE) FRUIT; ALOE VERA LEAF; HAMAMELIS VIRGINIANA TOP WATER

Active ingredients

Camphor 3%

Menthol 3%

Purpose

Topical Analgesic

Uses

Temporarily relieves the minor aches and pains of muscles and joints associated with:

- simple backache
- arthritis
- sprains
- bruises
- strains

Warnings

For external use only

When using this product

- use only as directed
- avoid contact with the eyes and mucous membranes
- do not apply to wounds or damaged, broken or irritated skin
- do not bandage tightly or apply local heat (such as heating pads) to the area of use

Stop use and ask a doctor if

- condition worsens, or symptoms persist for more than 7 days or clear up and occur again within a few days

PREGNANCY OR BREAST FEEDING

If pregnant or breast-feeding, ask a health professional before use.

Keep out of reach of children. If swallowed, get medical help or contact a Poison Control Center right away.

Directions

- adults and children 12 years of age and older: apply to affected area not more than 3 to 4 times daily
- children under 12 years of age: do not use, consult a physician
- wash hands after use with cool water

Other information

- store at 20-25°C (68-77°F)
- store in a cool, dry place away from direct sunlight

Inactive ingredients

Aloe Barbadensis Leaf Juice, Ananas Sativus (Pineapple) Fruit Extract, Arnica Montana Flower Extract, Benzoic Acid, Boswellia Carterii Resin Extract, Camellia Sinensis Flower Extract, Capsicum Annuum Extract, Carbomer, Decyl Glucoside, Glycerin, Hamamelis Virginiana (Witch Hazel) Water, Methyl Sulfonyl Methane, Phenoxyethanol, Propylene Glycol, Rosa Centifolia Flower Extract, Salix Alba (Willow) Bark Extract, Sodium Hydroxide, Sorbic Acid, Vitis Vinifera (Grape) Seed Extract, Water, Zingiber Officinale (Ginger) Root Extract

PACKAGE LABEL

Camphor 3% & Menthol 3%

PAIN RELIEVING CREAM

GOLDEN TIGER

with Arnica & Ginger

3 FL OZ (88.72 ML)